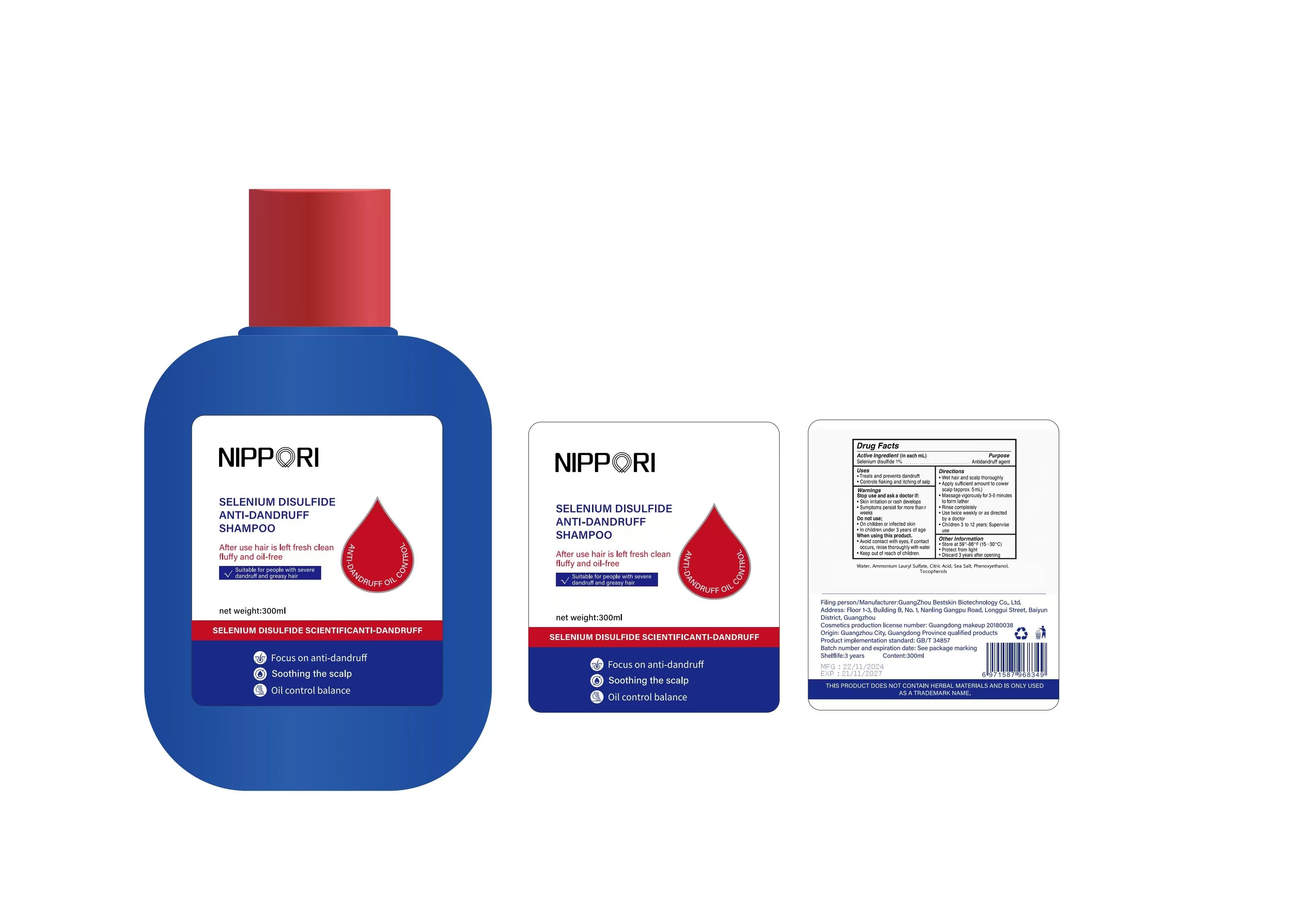 DRUG LABEL: SELENIUMDISULFIDEANTI-DANDRUFFSHAMPOO
NDC: 84778-080 | Form: LIQUID
Manufacturer: Guangzhou Yixin Cross-border E-commerce Co., Ltd.
Category: otc | Type: HUMAN OTC DRUG LABEL
Date: 20250827

ACTIVE INGREDIENTS: SELENIUM SULFIDE 1 g/100 g
INACTIVE INGREDIENTS: TOCOPHEROL; AMMONIUM LAURYL SULFATE; WATER; SEA SALT; PHENOXYETHANOL; CITRIC ACID

Active ingredients

Selenium disulfide 1%

Purpose

Antidandruff agent

Uses:

• Treats and prevents dandruff
• Controls flaking and itching of the scalp

Warnings

For external use only.

Flammable: Keep away from fire or flame

Dosage and administration

Adults and children 3 years and older:

Wet hair thoroughly
Apply amount to cover scalp (approx. 1 teaspoon)
Massage 3-5 minutes until lather forms
Rinse completely with water
Repeat twice weekly

Children under 3 years: Do not use

Do NOT use:

• On broken or inflamed skin
• In children under 3 years
• If allergic to selenium compounds

When using this product:

• Avoid contact with eyes (if occurs, rinse immediately)
• Discontinue use if vision changes occur

Stop use and ask a doctor if:

• Skin irritation or rash occurs
• Condition worsens or persists after 8 weeks

Keep out of reach of children.

Inactive ingredients

Water, Ammonium Lauryl Sulfate, Citric Acid, Sea Salt, Phenoxyethanol, Tocopherols